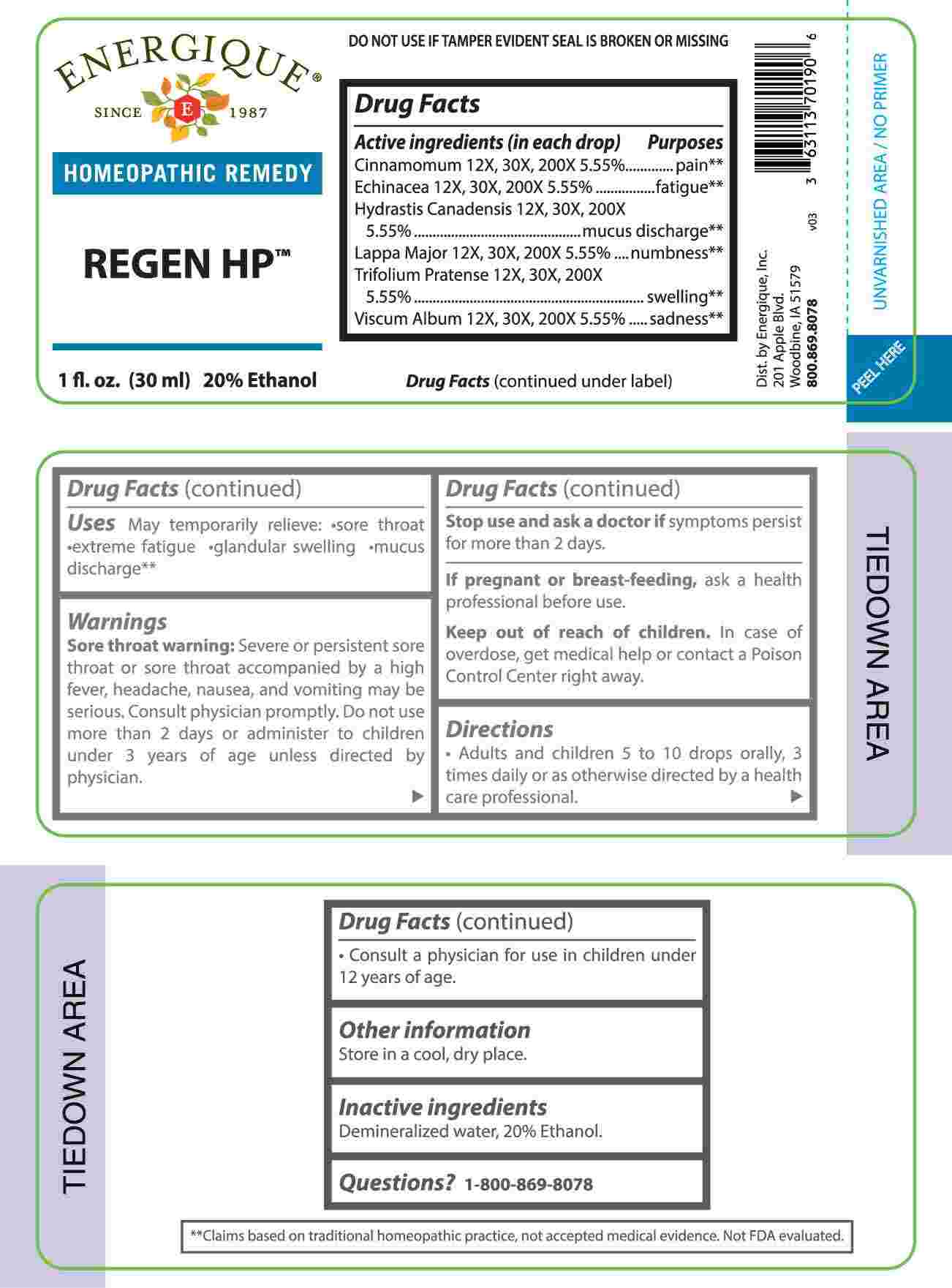 DRUG LABEL: Regen HP
NDC: 44911-0720 | Form: LIQUID
Manufacturer: Energique, Inc.
Category: homeopathic | Type: HUMAN OTC DRUG LABEL
Date: 20240924

ACTIVE INGREDIENTS: CINNAMON 12 [hp_X]/1 mL; ECHINACEA ANGUSTIFOLIA WHOLE 12 [hp_X]/1 mL; GOLDENSEAL 12 [hp_X]/1 mL; ARCTIUM LAPPA ROOT 12 [hp_X]/1 mL; TRIFOLIUM PRATENSE FLOWER 12 [hp_X]/1 mL; VISCUM ALBUM FRUITING TOP 12 [hp_X]/1 mL
INACTIVE INGREDIENTS: WATER; ALCOHOL

DRUG FACTS:

ACTIVE INGREDIENTS:

(in each drop) Cinnamomum 12X, 30X, 200X 5.55%, Echinacea 12X, 30X, 200X 5.55%, Hydrastis Canadensis 12X, 30X, 200X 5.55%, Lappa Major 12X, 30X, 200X 5.55%, Trifolium Pratense 12X, 30X, 200X 5.55%, Viscum Album 12X, 30X, 200X 5.55%.

PURPOSE:

Cinnamomum - pain,** Echinacea - fatigue,** Hydrastis Canadensis – mucus discharge,** Lappa Major - numbness,** Trifolium Pratense - swelling,** Viscum Album – sadness**

**Claims based on traditional homeopathic practice, not accepted medical evidence. Not FDA evaluated.

USES:

May temporarily relieve: •sore throat •extreme fatigue •glandular swelling •mucous discharge.**

**Claims based on traditional homeopathic practice, not accepted medical evidence. Not FDA evaluated.

WARNINGS:

Sore throat warning: Severe or persistent sore throat or sore throat accompanied by high fever, headache, nausea, and vomiting may be serious. Consult physician promptly. Do not use more than 2 days or administer to children under 3 years of age unless directed by a physician.

Stop use and ask a doctor if symptoms persist for more than 2 days.

If pregnant or breast-feeding, ask a health professional before use.

Keep out of reach of children. In case of overdose, get medical help or contact a Poison Control Center right away.

DO NOT USE IF TAMPER EVIDENT SEAL IS BROKEN OR MISSING

Store in a cool, dry place

KEEP OUT OF REACH OF CHILDREN:

In case of overdose, get medical help or contact a Poison Control Center right away.

DIRECTIONS:

• Adults and children 5 to 10 drops orally, 3 times daily or as otherwise directed by a health care professional.

• Consult a physician for use in children under 12 years of age.

INACTIVE INGREDIENTS:

Demineralized water, 20% Ethanol.

QUESTIONS:

Dist. by Energique, Inc.

201 Apple Blvd

Woodbine, IA 51579

800-869-8078

PACKAGE LABEL DISPLAY:

ENERGIQUE

SINCE 1987

HOMEOPATHIC REMEDY

REGEN HP

1 fl. oz. (30 ml)